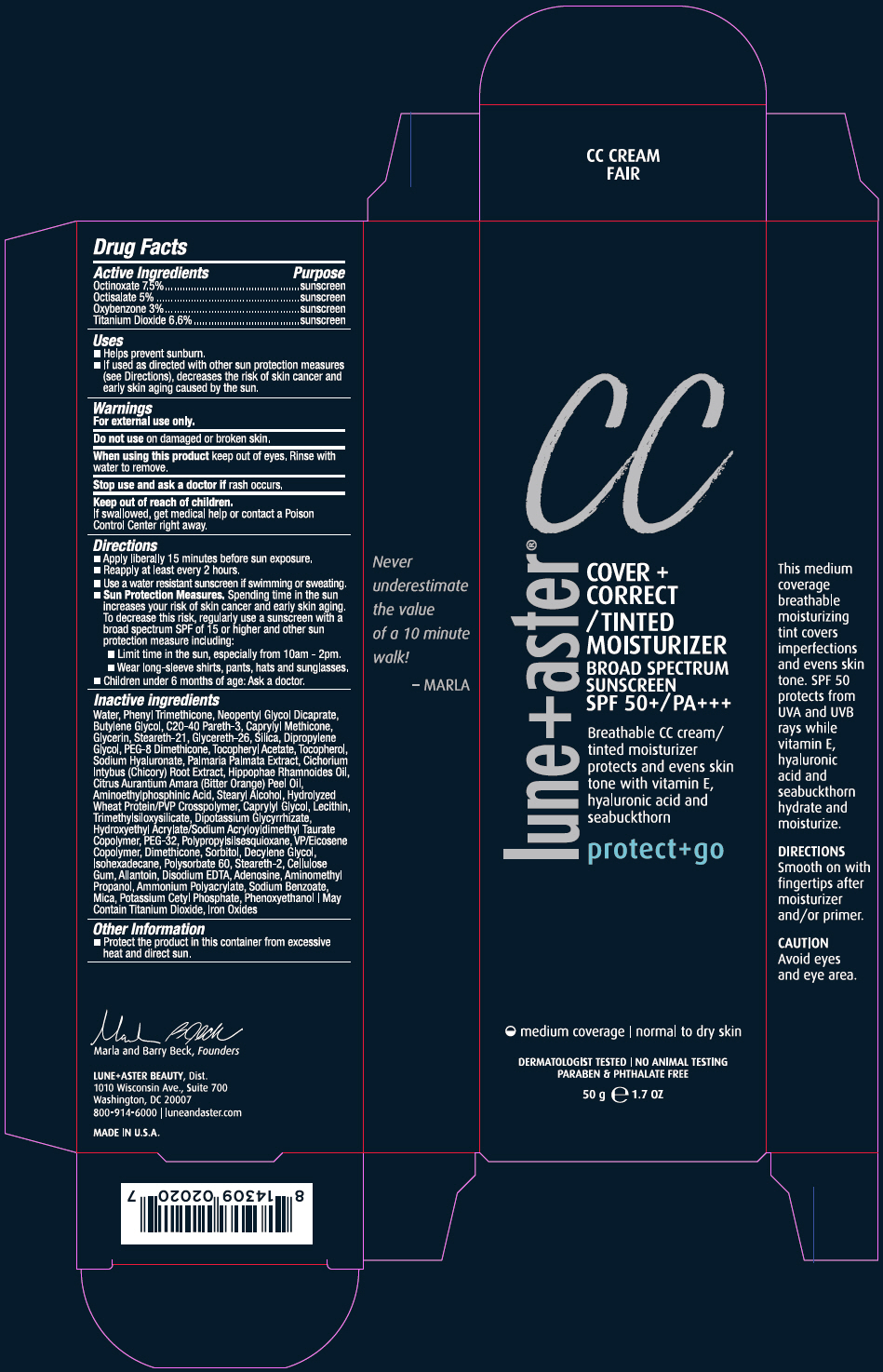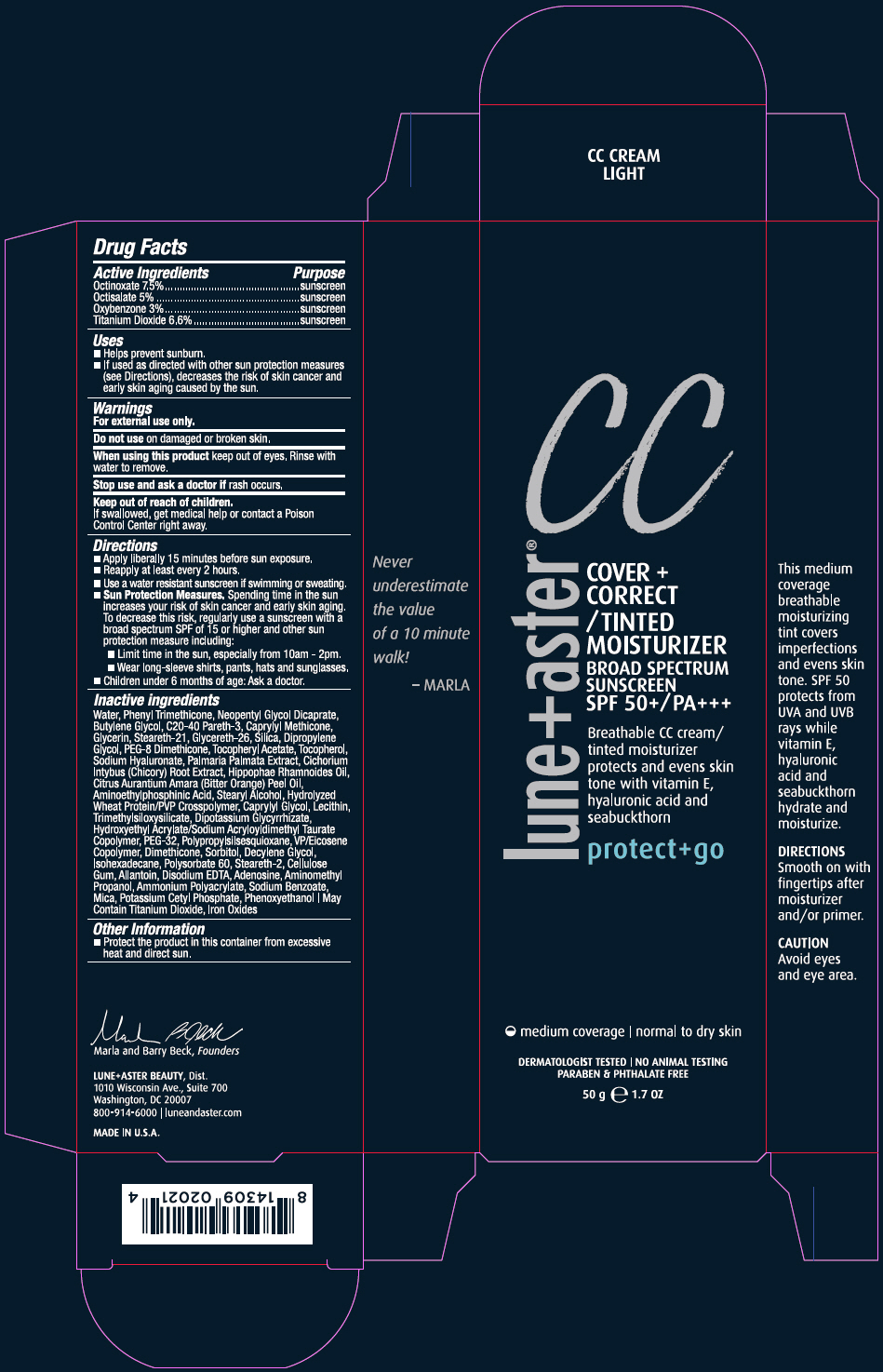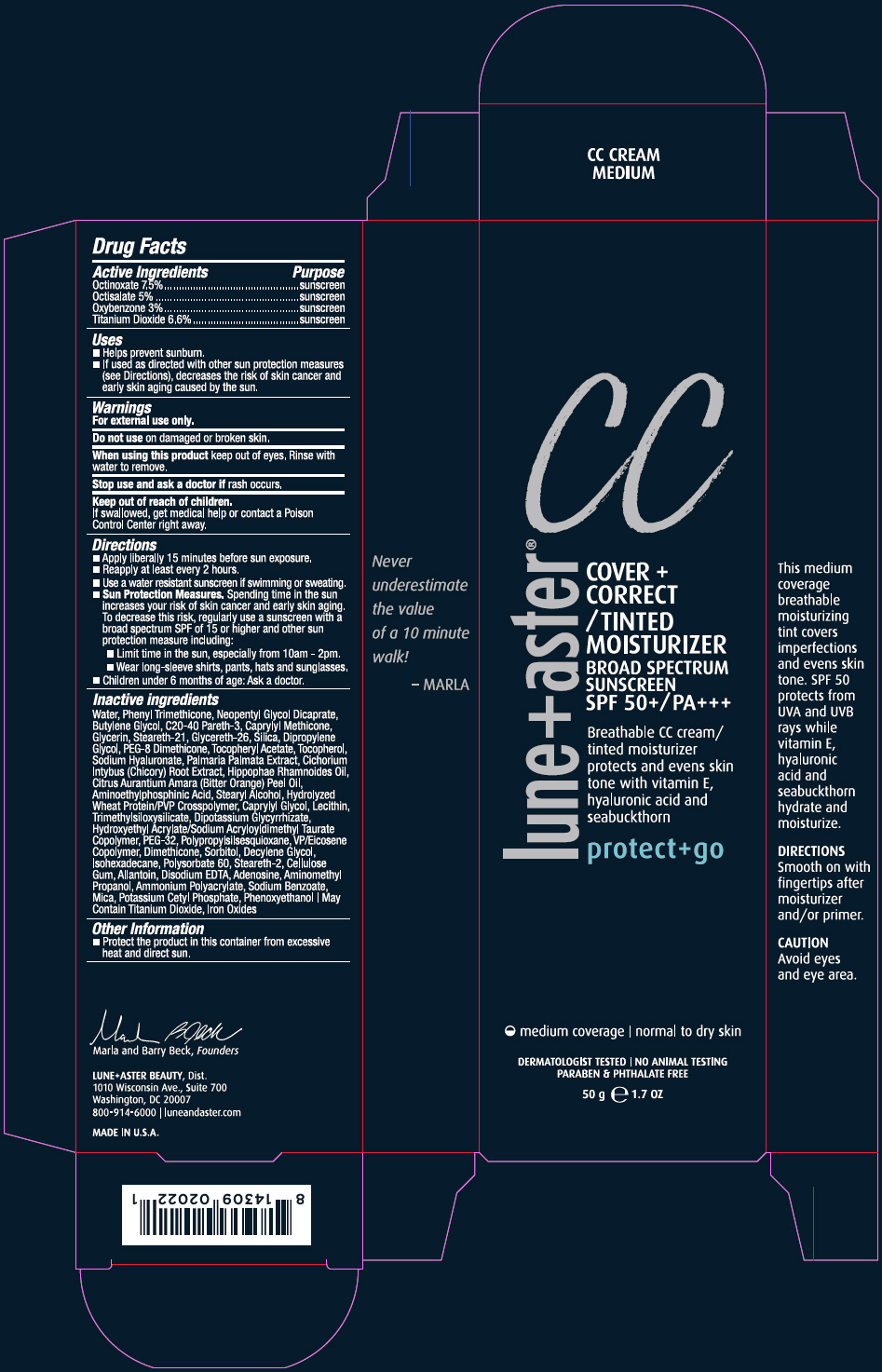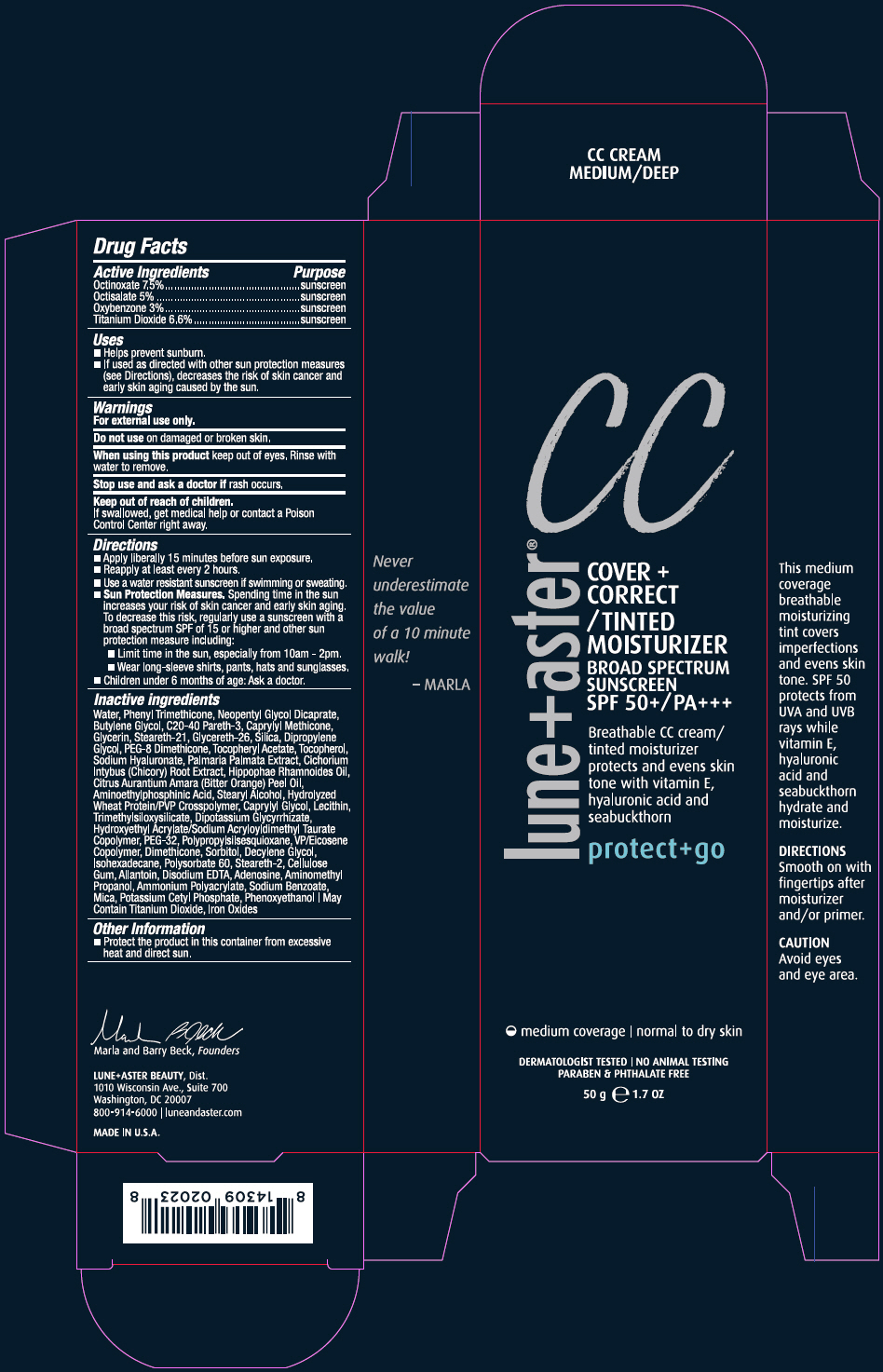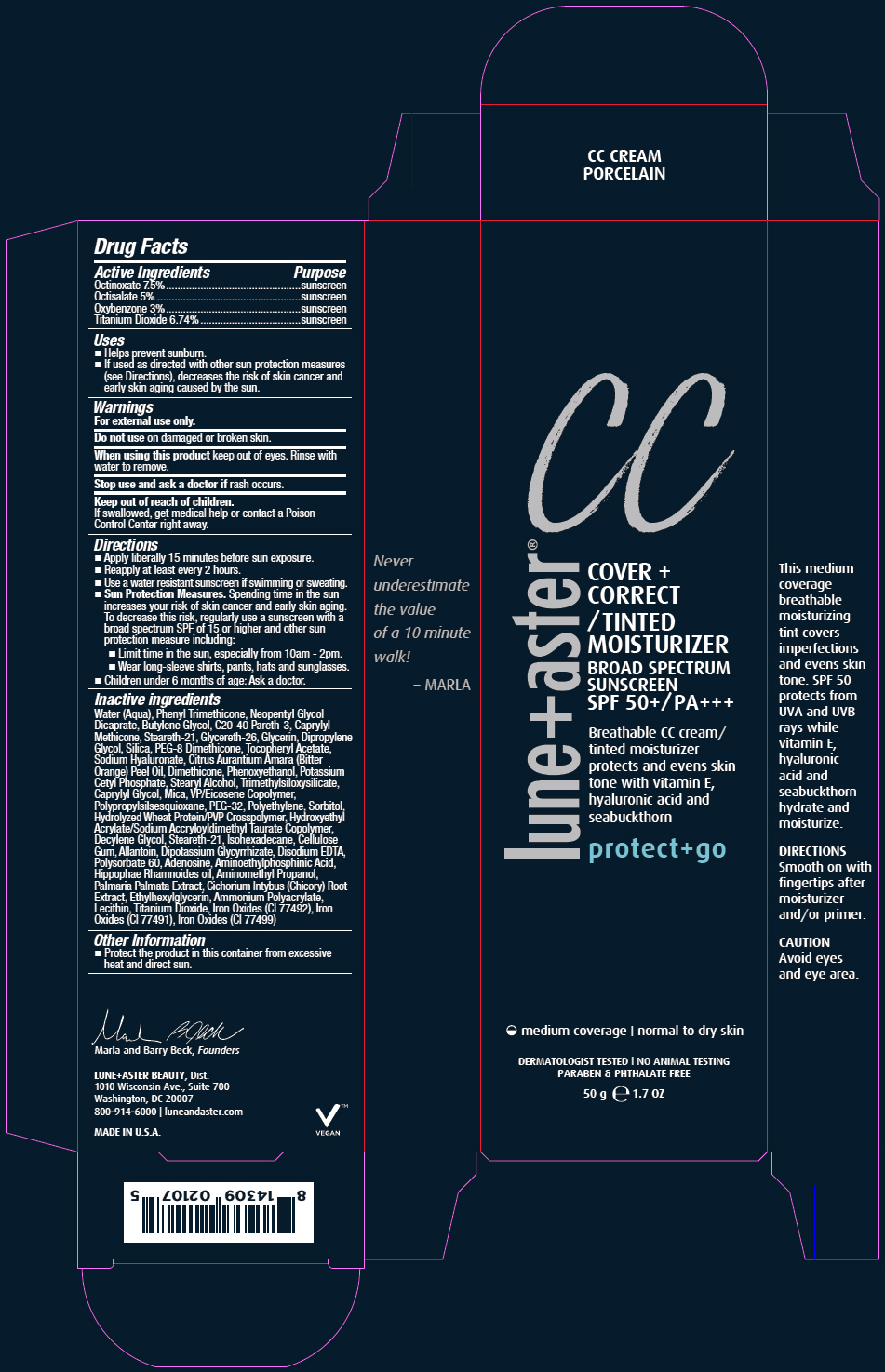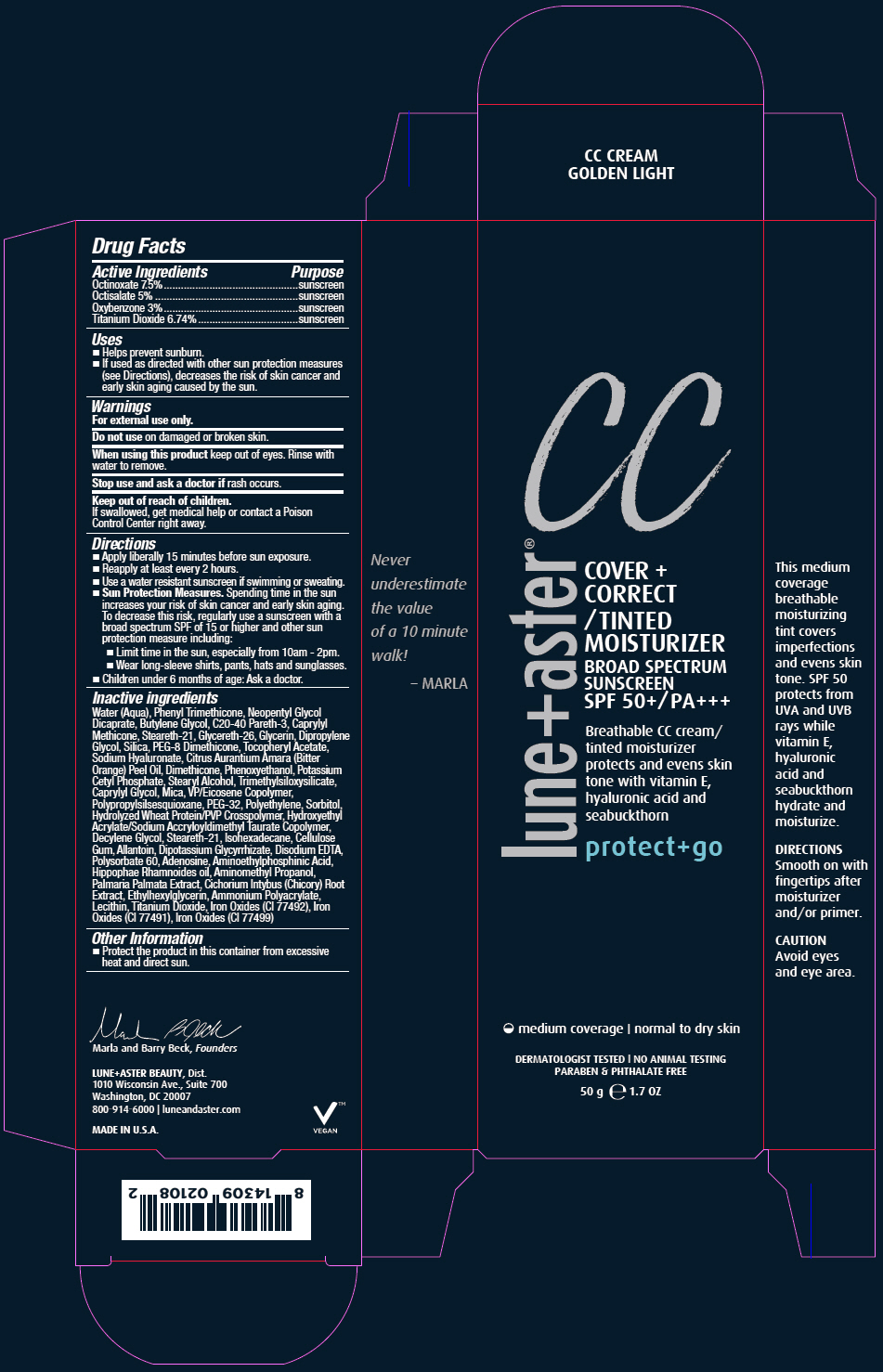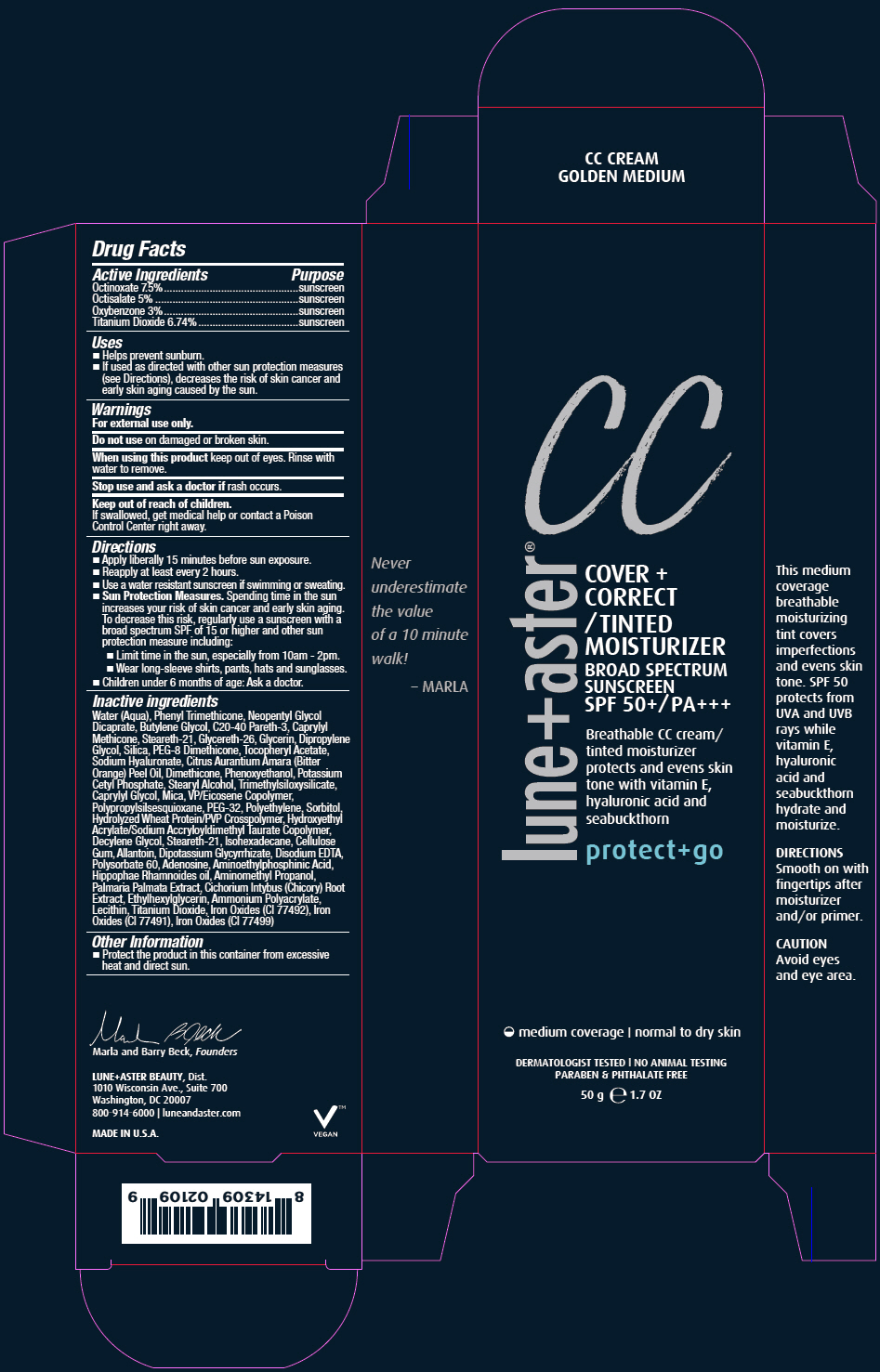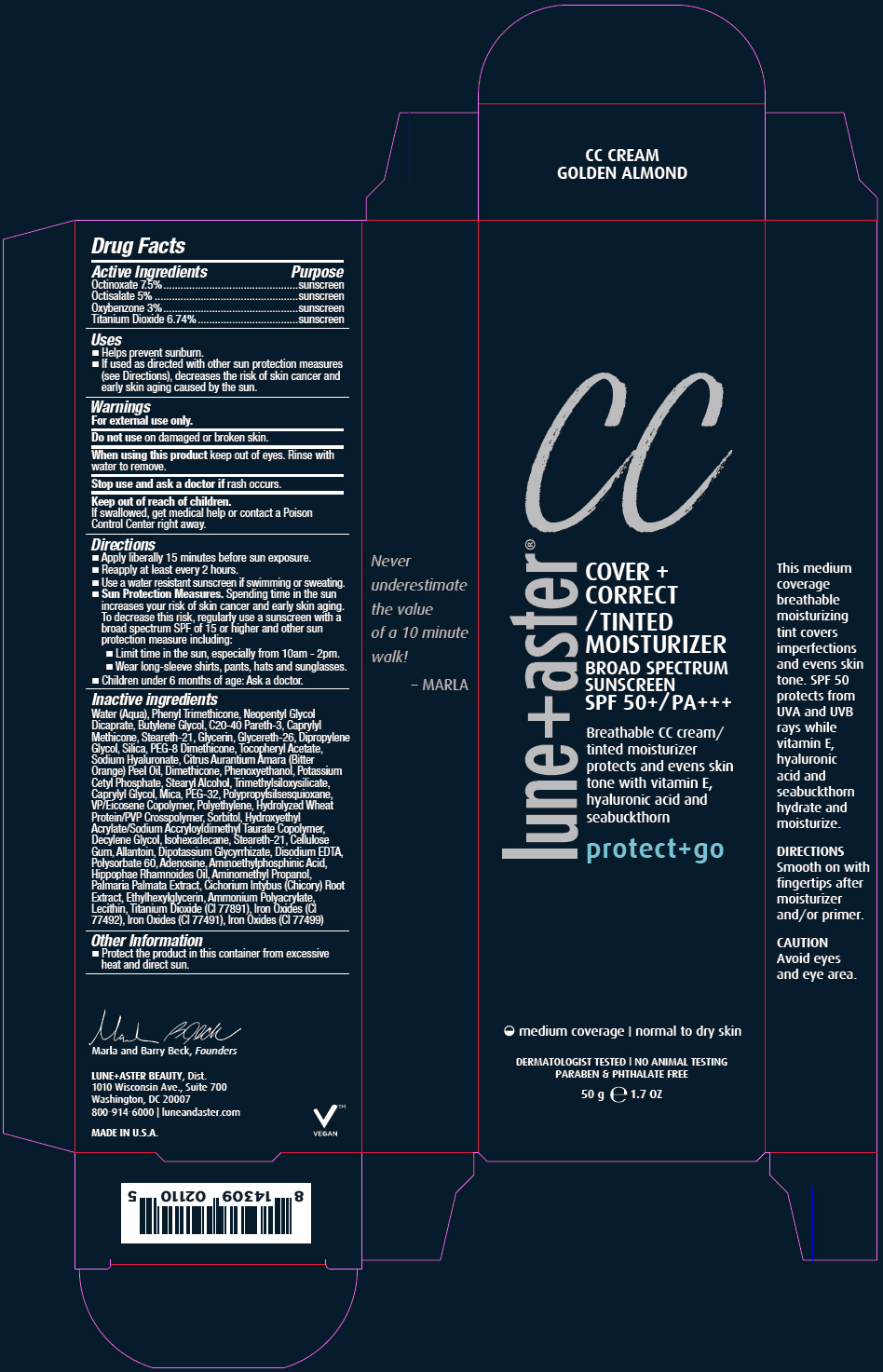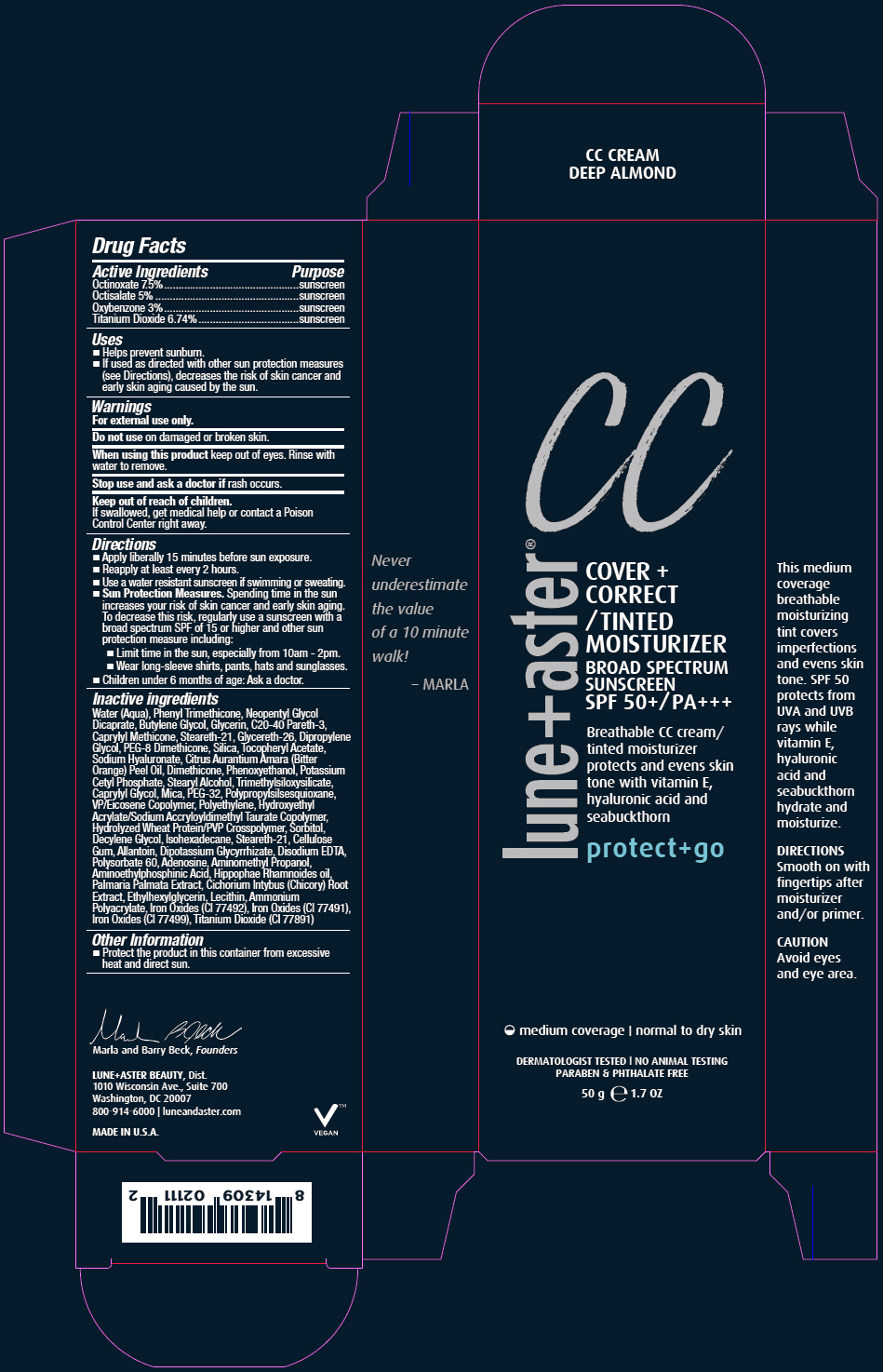 DRUG LABEL: COVER plus CORRECT/TINTED MOISTURIZER
NDC: 72203-005 | Form: CREAM
Manufacturer: Bluemercury
Category: otc | Type: HUMAN OTC DRUG LABEL
Date: 20250129

ACTIVE INGREDIENTS: OCTINOXATE 75 mg/1 g; OCTISALATE 50 mg/1 g; OXYBENZONE 30 mg/1 g; TITANIUM DIOXIDE 67.4 mg/1 g
INACTIVE INGREDIENTS: WATER; PHENYL TRIMETHICONE; NEOPENTYL GLYCOL DICAPRATE; BUTYLENE GLYCOL; GLYCERIN; C20-40 PARETH-3; CAPRYLYL TRISILOXANE; STEARETH-21; GLYCERETH-26; DIPROPYLENE GLYCOL; PEG-8 DIMETHICONE; SILICON DIOXIDE; HYALURONATE SODIUM; BITTER ORANGE OIL; DIMETHICONE; PHENOXYETHANOL; POTASSIUM CETYL PHOSPHATE; STEARYL ALCOHOL; CAPRYLYL GLYCOL; MICA; POLYETHYLENE GLYCOL 1600; HIGH DENSITY POLYETHYLENE; SORBITOL; DECYLENE GLYCOL; ISOHEXADECANE; CARBOXYMETHYLCELLULOSE SODIUM, UNSPECIFIED; ALLANTOIN; GLYCYRRHIZINATE DIPOTASSIUM; EDETATE DISODIUM ANHYDROUS; POLYSORBATE 60; ADENOSINE; AMINOMETHYLPROPANOL; AMINOETHYLPHOSPHINIC ACID; ETHYLHEXYLGLYCERIN; FERRIC OXIDE YELLOW; FERRIC OXIDE RED; FERROSOFERRIC OXIDE

COVER plus CORRECT/TINTED MOISTURIZER

Drug Facts

ACTIVE INGREDIENT

Active Ingredients | Purpose
Octinoxate 7.5% | sunscreen
Octisalate 5% | sunscreen
Oxybenzone 3% | sunscreen
Titanium Dioxide 6.74% | sunscreen

Uses

- Helps prevent sunburn.
- If used as directed with other sun protection measures (see Directions), decreases the risk of skin cancer and early skin aging caused by the sun.

Warnings

For external use only.

Do not useon damaged or broken skin.

WHEN USING

When using this productkeep out of eyes. Rinse with water to remove.

Stop use and ask a doctor ifrash occurs.

Keep out of reach of children.

If swallowed, get medical help or contact a Poison Control Center right away.

Directions

- Apply liberally 15 minutes before sun exposure.
- Reapply at least every 2 hours.
- Use a water resistant sunscreen if swimming or sweating.
- Sun Protection Measures.Spending time in the sun increases your risk of skin cancer and early skin aging. To decrease this risk, regularly use a sunscreen with a broad spectrum SPF of 15 or higher and other sun protection measure including:
  - Limit time in the sun, especially from 10am - 2pm.
  - Wear long-sleeve shirts, pants, hats and sunglasses.
- Children under 6 months of age: Ask a doctor.

Inactive ingredients

Water (Aqua), Phenyl Trimethicone, Neopentyl Glycol Dicaprate, Butylene Glycol, Glycerin, C20-40 Pareth-3, Caprylyl Methicone, Steareth-21, Glycereth-26, Dipropylene Glycol, PEG-8 Dimethicone, Silica, Tocopheryl Acetate, Sodium Hyaluronate, Citrus Aurantium Amara (Bitter Orange) Peel Oil, Dimethicone, Phenoxyethanol, Potassium Cetyl Phosphate, Stearyl Alcohol, Trimethylsiloxysilicate, Caprylyl Glycol, Mica, PEG-32, Polypropylsilsesquioxane, VP/Eicosene Copolymer, Polyethylene, Hydroxyethyl Acrylate/Sodium Accryloyldimethyl Taurate Copolymer, Hydrolyzed Wheat Protein/PVP Crosspolymer, Sorbitol, Decylene Glycol, Isohexadecane, Steareth-21, Cellulose Gum, Allantoin, Dipotassium Glycyrrhizate, Disodium EDTA, Polysorbate 60, Adenosine, Aminomethyl Propanol, Aminoethylphosphinic Acid, Hippophae Rhamnoides oil, Palmaria Palmata Extract, Cichorium Intybus (Chicory) Root Extract, Ethylhexylglycerin, Lecithin, Ammonium Polyacrylate, Iron Oxides (CI 77492), Iron Oxides (CI 77491), Iron Oxides (CI 77499), Titanium Dioxide (CI 77891)

Other Information

- Protect the product in this container from excessive heat and direct sun.

PRINCIPAL DISPLAY PANEL - 50 g Tube Carton - CC CRM FAIR

CC

lune+aster®
COVER +
CORRECT
/TINTED
MOISTURIZER
BROAD SPECTRUM
SUNSCREEN
SPF 50+/PA+++

Breathable CC cream/
tinted moisturizer
protects and evens skin
tone with vitamin E,
hyaluronic acid and
seabuckthorn

protect+go

medium coverage | normal to dry skin

DERMATOLOGIST TESTED | NO ANIMAL TESTING
PARABEN & PHTHALATE FREE

50 g e 1.7 OZ

PRINCIPAL DISPLAY PANEL - 50 g Tube Carton - CC CRM LIGHT

CC

lune+aster®
COVER +
CORRECT
/TINTED
MOISTURIZER
BROAD SPECTRUM
SUNSCREEN
SPF 50+/PA+++

Breathable CC cream/
tinted moisturizer
protects and evens skin
tone with vitamin E,
hyaluronic acid and
seabuckthorn

protect+go

medium coverage | normal to dry skin

DERMATOLOGIST TESTED | NO ANIMAL TESTING
PARABEN & PHTHALATE FREE

50 g e 1.7 OZ

PRINCIPAL DISPLAY PANEL - 50 g Tube Carton - CC CRM MED

CC

lune+aster®
COVER +
CORRECT
/TINTED
MOISTURIZER
BROAD SPECTRUM
SUNSCREEN
SPF 50+/PA+++

Breathable CC cream/
tinted moisturizer
protects and evens skin
tone with vitamin E,
hyaluronic acid and
seabuckthorn

protect+go

medium coverage | normal to dry skin

DERMATOLOGIST TESTED | NO ANIMAL TESTING
PARABEN & PHTHALATE FREE

50 g e 1.7 OZ

PRINCIPAL DISPLAY PANEL - 50 g Tube Carton - CC CRM MED/DEEP

CC

lune+aster®
COVER +
CORRECT
/TINTED
MOISTURIZER
BROAD SPECTRUM
SUNSCREEN
SPF 50+/PA+++

Breathable CC cream/
tinted moisturizer
protects and evens skin
tone with vitamin E,
hyaluronic acid and
seabuckthorn

protect+go

medium coverage | normal to dry skin

DERMATOLOGIST TESTED | NO ANIMAL TESTING
PARABEN & PHTHALATE FREE

50 g e 1.7 OZ

PRINCIPAL DISPLAY PANEL - 50 g Tube Carton - CC CRM PORCELAIN

CC

lune+aster®
COVER +
CORRECT
/TINTED
MOISTURIZER
BROAD SPECTRUM
SUNSCREEN
SPF 50+/PA+++

Breathable CC cream/
tinted moisturizer
protects and evens skin
tone with vitamin E,
hyaluronic acid and
seabuckthorn

protect+go

medium coverage | normal to dry skin

DERMATOLOGIST TESTED | NO ANIMAL TESTING
PARABEN & PHTHALATE FREE

50 g e 1.7 OZ

PRINCIPAL DISPLAY PANEL - 50 g Tube Carton - CC CRM GOLDEN LIGHT

CC

lune+aster®
COVER +
CORRECT
/TINTED
MOISTURIZER
BROAD SPECTRUM
SUNSCREEN
SPF 50+/PA+++

Breathable CC cream/
tinted moisturizer
protects and evens skin
tone with vitamin E,
hyaluronic acid and
seabuckthorn

protect+go

medium coverage | normal to dry skin

DERMATOLOGIST TESTED | NO ANIMAL TESTING
PARABEN & PHTHALATE FREE

50 g e 1.7 OZ

PRINCIPAL DISPLAY PANEL - 50 g Tube Carton - CC CRM GOLDEN MEDIUM

CC

lune+aster®
COVER +
CORRECT
/TINTED
MOISTURIZER
BROAD SPECTRUM
SUNSCREEN
SPF 50+/PA+++

Breathable CC cream/
tinted moisturizer
protects and evens skin
tone with vitamin E,
hyaluronic acid and
seabuckthorn

protect+go

medium coverage | normal to dry skin

DERMATOLOGIST TESTED | NO ANIMAL TESTING
PARABEN & PHTHALATE FREE

50 g e 1.7 OZ

PRINCIPAL DISPLAY PANEL - 50 g Tube Carton - CC CRM GOLDEN ALMOND

CC

lune+aster®
COVER +
CORRECT
/TINTED
MOISTURIZER
BROAD SPECTRUM
SUNSCREEN
SPF 50+/PA+++

Breathable CC cream/
tinted moisturizer
protects and evens skin
tone with vitamin E,
hyaluronic acid and
seabuckthorn

protect+go

medium coverage | normal to dry skin

DERMATOLOGIST TESTED | NO ANIMAL TESTING
PARABEN & PHTHALATE FREE

50 g e 1.7 OZ

PRINCIPAL DISPLAY PANEL - 50 g Tube Carton - CC CRM DEEP ALMOND

CC

lune+aster®
COVER +
CORRECT
/TINTED
MOISTURIZER
BROAD SPECTRUM
SUNSCREEN
SPF 50+/PA+++

Breathable CC cream/
tinted moisturizer
protects and evens skin
tone with vitamin E,
hyaluronic acid and
seabuckthorn

protect+go

medium coverage | normal to dry skin

DERMATOLOGIST TESTED | NO ANIMAL TESTING
PARABEN & PHTHALATE FREE

50 g e 1.7 OZ